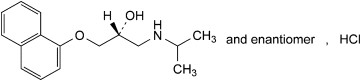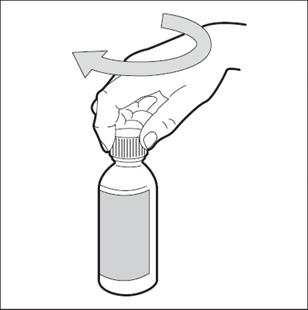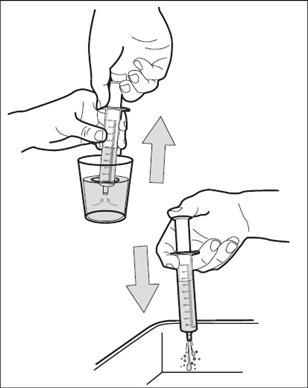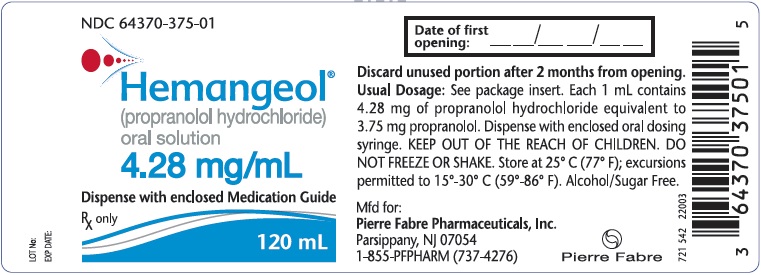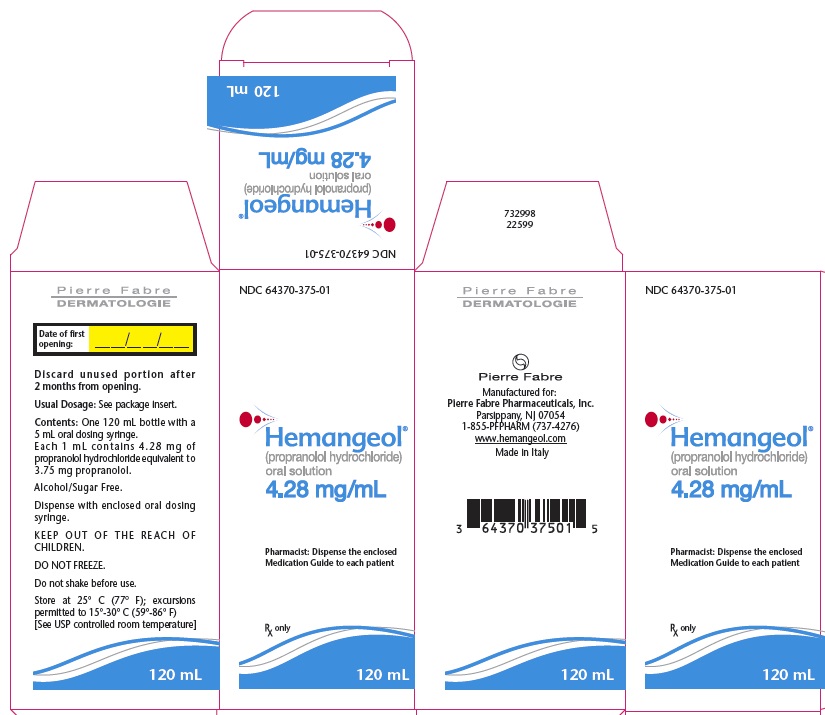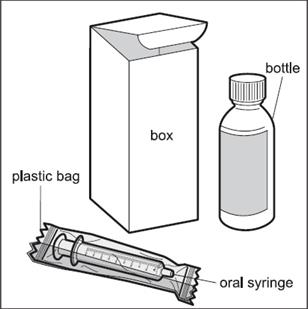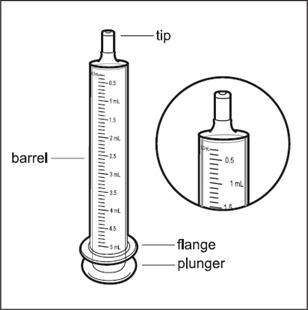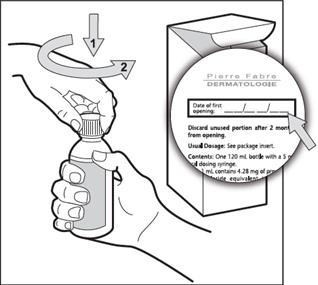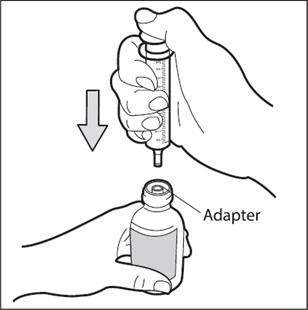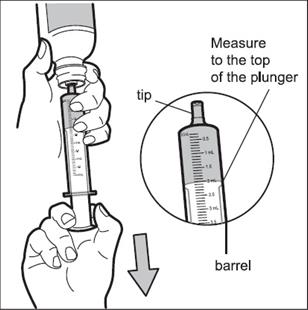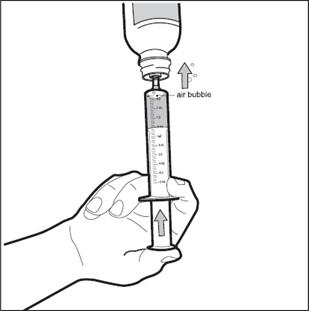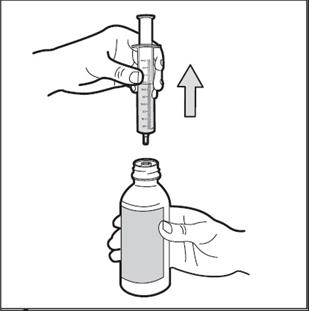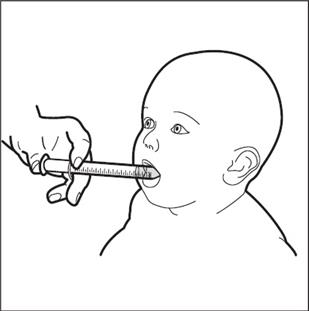 DRUG LABEL: HEMANGEOL
NDC: 64370-375 | Form: SOLUTION
Manufacturer: Pierre Fabre Pharmaceuticals, Inc.
Category: prescription | Type: HUMAN PRESCRIPTION DRUG LABEL
Date: 20251217

ACTIVE INGREDIENTS: PROPRANOLOL HYDROCHLORIDE 4.28 mg/1 mL

HIGHLIGHTS OF PRESCRIBING INFORMATION

HEMANGEOL® (propranolol hydrochloride oral solution)
These highlights do not include all the information needed to use HEMANGEOL safely and effectively. See full prescribing information for HEMANGEOL.
Initial U.S. Approval: 1967

1 INDICATIONS AND USAGE

HEMANGEOL oral solution is a beta-adrenergic blocker indicated for the treatment of proliferating infantile hemangioma requiring systemic therapy. (1)

2 DOSAGE AND ADMINISTRATION

- Initiate treatment at ages 5 weeks to 5 months. (2)
- Starting dose is 0.15 mL/kg (0.6 mg/kg) twice daily. After 1 week, increase dose to 0.3 mL/kg (1.1 mg/kg) twice daily. After 2 weeks, increase to a maintenance dose of 0.4 mL/kg (1.7 mg/kg) twice daily. (2)
- Administer doses at least 9 hours apart during or after feeding. (2)
- Readjust dose for changes in the child’s weight. (2)
- Monitor heart rate and blood pressure for 2 hours after the first dose or increasing dose. (2)

3 DOSAGE FORMS AND STRENGTHS

Oral solution: 4.28 mg/mL propranolol hydrochloride (3)

4 CONTRAINDICATIONS

- Premature infants with corrected age <5 weeks (4)
- Infants weighing less than 2 kg (4)
- Known hypersensitivity to propranolol or excipients (4)
- Asthma or history of bronchospasm (4, 5.3, 6, 10, 17)
- Bradycardia (<80 beats per minute), greater than first degree heart block, decompensated heart failure (4, 5.2, 5.4, 10, 17)
- Blood pressure <50/30 mmHg (4, 5.2, 10, 17)
- Pheochromocytoma (4)

5 WARNINGS AND PRECAUTIONS

Hypoglycemia: Administer during or after feeding. Do not use in patients who are not able to feed
or are vomiting (4, 5.1, 6, 10,17)
• Bradycardia and hypotension (4, 5.2, 17)
• Bronchospasm: Avoid use in patients with asthma or lower respiratory infection (4, 5.3, 6, 10, 17)
• Increased risk of stroke in PHACE syndrome (5.5)

6 ADVERSE REACTIONS

The most common adverse reactions to HEMANGEOL (occurring ≥ 10% of patients) were sleep disorders, aggravated respiratory tract infections, diarrhea, and vomiting. (6)

To report SUSPECTED ADVERSE REACTIONS, contact Pierre Fabre Pharmaceuticals, Inc. at 1-855-PFPHARM (737-4276) or FDA at 1-800-FDA-1088 or www.fda.gov/medwatch.

See 17 for PATIENT COUNSELING INFORMATION and Medication Guide

FULL PRESCRIBING INFORMATION

1 INDICATIONS AND USAGE

HEMANGEOL oral solution contains the beta-adrenergic blocker propranolol hydrochloride and is indicated for the treatment of proliferating infantile hemangioma requiring systemic therapy.

2 DOSAGE AND ADMINISTRATION

Initiate treatment at ages 5 weeks to 5 months.

The recommended starting dose of HEMANGEOL is 0.15 mL/kg (0.6 mg/kg) (see Table 1) twice daily, taken at least 9 hours apart. After 1 week, increase the daily dose to 0.3 mL/kg (1.1 mg/kg) twice daily. After 2 weeks of treatment, increase the dose to 0.4 mL/kg (1.7 mg/kg) twice daily and maintain this for 6 months. Readjust the dose periodically as the child’s weight increases.

To reduce the risk of hypoglycemia, administer HEMANGEOL orally during or right after a feeding. Skip the dose if the child is not eating or is vomiting [see Warnings and Precautions (5.1)] .

Monitor heart rate and blood pressure for 2 hours after HEMANGEOL initiation or dose increases [see Warnings and Precautions (5.2)].

If hemangiomas recur, treatment may be re-initiated [see Clinical Studies (14)] .

HEMANGEOL is supplied with an oral dosing syringe for administration. Administration directly into the child’s mouth is recommended. Nevertheless, if necessary, the product may be diluted in a small quantity of milk or fruit juice, given in a baby’s bottle.

Table 1. Dose Titration According to Weight

 | Week 1 | Week 2 | Week 3 (maintenance)
Weight (kg) | Volume administered | Volume administered | Volume administered
Weight (kg) | twice a day | twice a day | twice a day
2 to <2.5 | 0.3 mL | 0.6 mL | 0.8 mL
2.5 to <3 | 0.4 mL | 0.8 mL | 1 mL
3 to <3.5 | 0.5 mL | 0.9 mL | 1.2 mL
3.5 to <4 | 0.5 mL | 1.1 mL | 1.4 mL
4 to <4.5 | 0.6 mL | 1.2 mL | 1.6 mL
4.5 to <5 | 0.7 mL | 1.4 mL | 1.8 mL
5 to <5.5 | 0.8 mL | 1.5 mL | 2 mL
5.5 to <6 | 0.8 mL | 1.7 mL | 2.2 mL
6 to <6.5 | 0.9 mL | 1.8 mL | 2.4 mL
6.5 to <7 | 1 mL | 2 mL | 2.6 mL
7 to <7.5 | 1.1 mL | 2.1 mL | 2.8 mL
7.5 to <8 | 1.1 mL | 2.3 mL | 3 mL
8 to <8.5 | 1.2 mL | 2.4 mL | 3.2 mL
8.5 to <9 | 1.3 mL | 2.6 mL | 3.4 mL
9 to <9.5 | 1.4 mL | 2.7 mL | 3.6 mL
9.5 to <10 | 1.4 mL | 2.9 mL | 3.8 mL
10 to <10.5 | 1.5 mL | 3 mL | 4 mL
10.5 to <11 | 1.6 mL | 3.2 mL | 4.2 mL
11 to <11.5 | 1.7 mL | 3.3 mL | 4.4 mL
11.5 to <12 | 1.7 mL | 3.5 mL | 4.6 mL
12 to <12.5 | 1.8 mL | 3.6 mL | 4.8 mL

3 DOSAGE FORMS AND STRENGTHS

Oral solution: 4.28 mg/mL propranolol hydrochloride.

Alcohol-, paraben- and sugar-free.

4 CONTRAINDICATIONS

HEMANGEOL is contraindicated in the following conditions:

- Premature infants with corrected age < 5 weeks
- Infants weighing less than 2 kg
- Known hypersensitivity to propranolol or any of the excipients [see Description (11)]
- Asthma or history of bronchospasm
- Heart rate <80 beats per minute, greater than first degree heart block, or decompensated heart failure
- Blood pressure <50/30 mmHg
- Pheochromocytoma

5 WARNINGS AND PRECAUTIONS

5.1 Hypoglycemia

HEMANGEOL prevents the response of endogenous catecholamines to correct hypoglycemia and masks the adrenergic warning signs of hypoglycemia, particularly tachycardia, palpitations and sweating. HEMANGEOL can cause hypoglycemia at any time during treatment. Risk is increased during a fasting period (e.g., poor oral food intake, infection, vomiting) or when glucose demands are increased (e.g., cold, stress, infections). Withhold the dose under these conditions. Hypoglycemia may present in
the form of seizures, lethargy, or coma. Discontinue HEMANGEOL if hypoglycemia develops and treat appropriately Concomitant treatment with corticosteroids may increase the risk of hypoglycemia [ see Drug Interactions (7) ] .

5.2 Bradycardia and Hypotension

HEMANGEOL may cause or worsen bradycardia or hypotension. In the studies of HEMANGEOL for infantile hemangioma the mean decrease in heart rate was about 7 bpm with little effect on blood pressure. Monitor heart rate and blood pressure after treatment initiation or increase in dose. Discontinue treatment if severe (<80 beats per minute) or symptomatic bradycardia or hypotension (systolic blood pressure <50 mmHg) occurs.

5.3 Bronchospasm

HEMANGEOL can cause bronchospasm; do not use in patients with asthma or a history of bronchospasm. Interrupt treatment in the event of a lower respiratory tract infection associated with dyspnea and wheezing.

5.4 Cardiac Failure

Sympathetic stimulation supports circulatory function in patients with congestive heart failure, beta blockade may precipitate more severe failure.

5.5 Increased Risk of Stroke in PHACE Syndrome

By dropping blood pressure, HEMANGEOL may increase the risk of stroke in PHACE syndrome patients with severe cerebrovascular anomalies.
Investigate infants with large facial infantile hemangioma for potential arteriopathy associated with PHACE syndrome prior to HEMANGEOL therapy.

5.6 Hypersensitivity

Beta-blockers will interfere with epinephrine used to treat serious anaphylaxis.

6 ADVERSE REACTIONS

The following serious adverse reactions are discussed in greater detail in other sections of the labeling:

- Hypoglycemia and related events, like hypoglycemic seizure [see Warnings and Precautions (5.1)].
- Bronchospasm [see Warnings and Precautions (5.3)].

6.1 Clinical Trials Experience

Because clinical trials are conducted under widely varying conditions, adverse reaction rates observed in the clinical
trials of a drug may not reflect the rates observed in clinical practice.

Clinical Trials Experience with HEMANGEOL in Infants with proliferating infantile hemangioma
In clinical trials for proliferating infantile hemangioma, the most frequently reported adverse reactions (>10%) in infants treated with HEMANGEOL were sleep disorders, aggravated respiratory tract infections such as bronchitis and bronchiolitis associated with cough and fever, diarrhea, and vomiting. Adverse reactions led to treatment discontinuation in fewer than 2% of treated patients.

Overall, 479 patients in the pooled safety population were exposed to study drug in the clinical study program (456 in placebo-controlled trials). A total of 424 patients were treated with HEMANGEOL at doses 1.2 mg/kg/day or 3.4 mg/kg/day for 3 or 6 months. Of these, 63% of patients were aged 91-150 days and 37% were aged 35-90 days at randomization.

The following table lists according to the dosage the most common adverse reactions (treatment-emergent adverse events with an incidence at least 3% greater on one of the two doses than on placebo).

Table 2. Treatment-emergent adverse events occurring at least 3% more often on HEMANGEOL than on placebo

Reaction | Placebo N=236 | HEMANGEOL 1.2 mg/kg/day N=200 | HEMANGEOL 3.4 mg/kg/day N=224
Sleep disorder | 5.9% | 17.5% | 16.1%
Bronchitis | 4.7 | 8.0 | 13.4
Peripheral coldness | 0.4 | 8.0 | 6.7
Agitation | 2.1 | 8.5 | 4.5
Diarrhea | 1.3 | 4.5 | 6.3
Somnolence | 0.4 | 5.0 | 0.9
Nightmare | 1.7 | 2.0 | 6.3
Irritability | 1.3 | 5.5 | 1.3
Decreased appetite | 0.4 | 2.5 | 3.6
Abdominal pain | 0.4 | 3.5 | 0.4

The following adverse events have been observed during clinical studies, with an incidence of less than 1%:

Cardiac disorders: Second degree atrioventricular heart block, in a patient with underlying conduction disorder, required definitive treatment discontinuation [see Warnings and Precautions (5.4)] .

Skin and subcutaneous tissue disorders: Urticaria, alopecia

Investigations: Decreased blood glucose, decreased heart rate

Compassionate Use Program

More than 600 infants received HEMANGEOL in a compassionate use program (CUP). Mean age at treatment initiation was 3.6 months. Mean dose of HEMANGEOL was 2.2 mg/kg/day and mean treatment duration was 7.1 months.

The adverse reactions reported in the CUP were similar to the ADRs observed during clinical trials but some were more severe.

6.2 Postmarketing Experience

The following adverse reactions have been identified during post-approval use of propranolol. Because these reactions are reported voluntarily from a population of uncertain size, it is not always possible to reliably estimate their frequency or establish a causal relationship to drug exposure.

These adverse reactions are as follows:

Blood and lymphatic system disorders: Agranulocytosis

Psychiatric disorders: Hallucination

Skin and subcutaneous tissues disorders: Purpura, dermatitis psoriasform

7 DRUG INTERACTIONS

In the absence of specific studies in children, the drug interactions with propranolol are those known in adults. Consider both the infant’s medications and those of a nursing mother.

Pharmacokinetic drug interactions

Impact of co-administered drugs on propranolol: CYP2D6, CYP1A2 or CYP2C19 inhibitors increase propranolol plasma concentration. CYP1A2 inducers (phenytoin, phenobarbital) or CYP2C19 inducers (rifampin) decrease propranolol plasma concentration when co-administered.

Pharmacodynamic drug interactions

Corticosteroids: Patients on corticosteroids may be at increased risk of hypoglycemia because of loss of the counter-regulatory cortisol response; monitor patients for signs of hypoglycemia.

8 USE IN SPECIFIC POPULATIONS

8.4 Pediatric Use

Of 460 infants with proliferating infantile hemangioma requiring systemic therapy who were treated with HEMANGEOL starting at 5 weeks to 5 months of age, 60% had complete or nearly complete resolution of their hemangioma at Week 24 [see Clinical Studies (14)].

Safety and effectiveness for infantile hemangioma have not been established in pediatric patients greater than 1 year of age.

8.6 Hepatic Impairment

There is no experience in infants with hepatic impairment .

8.7 Renal Impairment

There is no experience in infants with renal impairment .

10 OVERDOSAGE

Few cases of propranolol overdose were reported. For a single intake, the maximum dose was 20 mg/kg. Symptomatic cases featured hypotension, hypoglycemic seizure, and restlessness/euphory/insomnia; for most cases, propranolol was maintained or reintroduced.

The toxicity of beta-blockers is an extension of their therapeutic effects:

- Cardiac symptoms of mild to moderate poisoning are decreased heart rate and hypotension. Atrioventricular blocks, intraventricular conduction delays, and congestive heart failure can occur with more severe poisoning.

- Bronchospasm may develop particularly in patients with asthma.

- Hypoglycemia may develop and manifestations of hypoglycemia (tremor, tachycardia) may be masked by other clinical effects of beta-blocker toxicity.

Support and treatment: Place the patient on a cardiac monitor, and monitor vital signs, mental status and blood glucose. Give intravenous fluids for hypotension and atropine for bradycardia. Glucagon then catecholamines should be considered if the patient does not respond appropriately to IV fluid. Isoproterenol and aminophylline may be used for bronchospasm.

Propranolol is not dialyzable.

11 DESCRIPTION

HEMANGEOL is an oral solution of propranolol that is alcohol free, paraben free and sugar free. Each mL of HEMANGEOL contains 4.28 mg of propranolol hydrochloride, USP equivalent to 3.75 mg of propranolol.

Propranolol hydrochloride is a synthetic beta-adrenergic receptor blocking agent chemically described as (2RS)1-[(1-methylethyl)amino]-3-(naphthalene-1-yloxy)-propan-2-ol hydrochloride. Its structural formula is shown in Figure 1:

Figure 1. Propranolol HCl Structure

Molecular formula: C16H21NO2-HCl

Propranolol hydrochloride is a stable, white, crystalline solid with a molecular weight of 295.8. It is readily soluble in water and ethanol.

HEMANGEOL contains the following inactive ingredients: strawberry/vanilla flavorings, hydroxyethylcellulose, saccharin sodium, citric acid monohydrate, and water.

12 CLINICAL PHARMACOLOGY

12.1 Mechanism of Action

The mechanism of HEMANGEOL’s effects on infantile hemangiomas is not well understood.

12.2 Pharmacodynamics

Propranolol is a nonselective beta-adrenergic receptor blocking agent possessing no other autonomic nervous system activity. It specifically competes with beta-adrenergic receptor stimulating agents for available receptor sites. When access to beta-receptor sites is blocked by propranolol, chronotropic, inotropic, and vasodilator responses to beta-adrenergic stimulation are decreased proportionately.

Propranolol selectively blocks beta-adrenergic receptors, leaving alpha-adrenergic responses intact. There are two well-characterized subtypes of beta receptors (beta1 and beta2); propranolol interacts with both subtypes equally.

Beta1-adrenergic receptors are found primarily in the heart. Blockade of cardiac beta1-adrenergic receptors leads to a decrease in the activity of both normal and ectopic pacemaker cells and a decrease in A-V nodal conduction velocity. Blockade of cardiac beta1-adrenergic receptors also decreases the myocardial force of contraction and may provoke cardiac decompensation in patients with minimal cardiac reserve.

Beta2-adrenergic receptors are found predominantly in smooth muscle-vascular, bronchial, gastrointestinal and genitourinary. Blockade of these receptors results in constriction. Propranolol’s beta-blocking effects are attributable to its S(-) enantiomer.

Pharmacodynamic drug interactions

Alpha blockers: Co-administration of beta-blockers with alpha blockers (prazosin) has been associated with prolongation of first dose hypotension and syncope.

Antidepressants: The hypotensive effect of MAO inhibitors and tricyclic antidepressants is exacerbated when administered with beta-blockers.

Nonsteroidal anti-inflammatory drugs: Nonsteroidal anti-inflammatory drugs (NSAIDs) may attenuate the antihypertensive effect of beta-adrenoreceptor blocking agents. Monitor blood pressure.

12.3 Pharmacokinetics

Adults

Absorption: Propranolol is almost completely absorbed after oral administration. However, it undergoes an extensive first-pass metabolism by the liver and on average; only about 25% of propranolol reaches the systemic circulation. Peak plasma concentrations occur about 1 to 4 hours after an oral dose. Administration of protein-rich foods increases the bioavailability of propranolol by about 50% with no change in time to peak concentration.

Propranolol is a substrate for the intestinal efflux transporter, P-glycoprotein (P-gp). However, studies suggest that P-gp is not dose-limiting for intestinal absorption of propranolol in the usual therapeutic dose range.

Distribution: Approximately 90% of circulating propranolol is bound to plasma proteins (albumin and alpha1 acid glycoprotein). The volume of distribution of propranolol is approximately 4 L/kg. Propranolol crosses the blood-brain barrier and the placenta, and is distributed into breast milk.

Propranolol is extensively metabolized with most metabolites appearing in the urine.

Metabolism: Propranolol is metabolized through three primary routes: aromatic hydroxylation (mainly 4-hydroxylation), N-dealkylation followed by further side-chain oxidation, and direct glucuronidation. The percentage contributions of these routes to total metabolism are 42%, 41% and 17%, respectively, but with considerable variability between individuals. The four major final metabolites are propranolol glucuronide, naphthyloxylactic acid and glucuronic acid, and sulfate conjugates of 4-hydroxy propranolol. In vitro studies indicated that CYP2D6 (aromatic hydroxylation), CYP1A2 (chain oxidation) and to a less extent CYP2C19 were involved in propranolol metabolism.

In healthy subjects, no difference was observed between CYP2D6 extensive metabolizers (EMs) and poor metabolizers (PMs) with respect to oral clearance or elimination half-life.

Elimination:The plasma half-life of propranolol ranges from 3 to 6 hours. Less than 1% of a dose is excreted as unchanged drug in the urine.

Infants

The pharmacokinetics of propranolol and 4-OH-propranolol were evaluated in a multiple dose 12 week study conducted in 23 male and female infants 35 to 150 days of age with hemangioma. The infants were stratified by age (35 to 90 days and 91 to 150 days). The starting dose was 1.2 mg/kg/day which was titrated to the target dose of 3.4 mg/kg/day in 1.1 mg/kg/day increments at weekly intervals. At steady state, following administration of 3.4 mg/kg/day twice daily, peak plasma propranolol concentrations were observed within 2 hours of oral administration. Clearance of propranolol in infants was similar across the age range studied (2.7 (SD=0.03) L/h/kg in infants <90 days of age and 3.3 (SD=0.35) L/h/kg in infants >90 days of age) and to that in adults when adjusted by body weight. The median elimination half-life of propranolol was about 3.5 hours. Plasma propranolol concentrations approximate a dose proportional increase in the dose range of 1.2 mg/kg/day to 3.4 mg/kg/day.

Plasma concentration of 4-OH-propranolol, the main metabolite, was about 5% of total plasma exposure of propranolol.

Sex

There is no known dependence of pharmacokinetics of propranolol by sex in infants.

Race

There is little information on dependence of pharmacokinetics of propranolol by race in infants.

A study conducted in 12 Caucasian and 13 African-American adult male subjects taking propranolol, showed that at steady state, the clearance of R(+)- and S(-)-propranolol were about 76% and 53% higher in African-Americans than in Caucasians, respectively.

Chinese adult subjects had a greater proportion (18% to 45% higher) of unbound propranolol in plasma compared to Caucasians, which was associated with a lower plasma concentration of alpha1 acid glycoprotein.

Drug Interaction Studies

Impact of propranolol on co-administered drugs: The effect of propranolol on plasma concentration of co-administered drug is presented in the table below.

Table 3. Effect of propranolol on co-administered drugs

Co-administered drug | Effect on plasma concentration of co-administered drug
Amide anesthetics (lidocaine, bupivacaine, mepivacaine) | Increase
Warfarin | Increase
Propafenone | Increase > 200 %
Nifedipine | Increase 80 %
Verapamil | No change
Pravastatin, lovastatin | Decrease 20%
Fluvastatin | No change
Zolmitriptan | Increase 60 %
Rizatriptan | Increase 80 %
Thioridazine | Increase 370 %
Diazepam | Increase
Oxazepam, triazolam, lorazepam, alprazolam | No change
Theophylline | Increase 70 %

Impact of co-administered drugs on propranolol: The effect of co-administered drugs on propranolol plasma concentration is presented in the table below.

Table 4. Effect of co-administered drugs on propranolol

Co-administered drug | Effect on propranolol plasma concentration
CYP2D6, CYP1A2 or CYP2C19 inhibitors | Increase
CYP1A2 or CYP2C19 inducers | Decrease
Quinidine | Increase > 200 %
Nisoldipine | Increase 50 %
Nicardipine | Increase 80 %
Chlorpromazine | Increase 70 %
Cimetidine | Increase 50 %
Cholestyramine, colestipol | Decrease 50 %
Alcohol | Increase (acute use), decrease (chronic use)
Diazepam | No change
Verapamil | No change
Metoclopramide | No change
Ranitidine | No change
Lansoprazole | No change
Omeprazole | No change
Propafenone | Increase 200 %
Aluminum hydroxide | Decrease 50 %

13 NONCLINICAL TOXICOLOGY

13.1 Carcinogenesis and Mutagenesis and Impairment of Fertility

In studies of mice and rats fed propranolol hydrochloride for up to 18 months at doses of up to 150 mg/kg/day, there was no evidence of drug-related tumorigenesis. On a body surface area basis, this dose in the mouse and rat is about 3 and 7 times, respectively, the MRHD of 3.4 mg/kg/day propranolol hydrochloride in children.

Based on differing results from bacterial reverse mutation (Ames) tests performed by different laboratories, there is equivocal evidence for mutagenicity in one strain (S. typhimurium strain TA 1538).

In a study in which both male and female rats were exposed to propranolol hydrochloride via diet at concentrations of up to 0.05% (about 50 mg/kg or less than the MRHD of 640 mg propranolol hydrochloride in adults) started from 60 days prior to mating and throughout pregnancy and lactation for two generations, there were no effects on fertility. The potential effects of propranolol hydrochloride on fertility of juvenile rats were evaluated following daily oral administration from post-natal Day 4 (PND 4) to PND 21 at dose-levels of 0, 11.4, 22.8 or 45.6 mg/kg/day. No propranolol related effects on reproductive parameters or reproductive development were observed up to the highest dose level of 45.6 mg/kg/day, a dose that represents a systemic exposure of 3 times that seen in children at the MRHD.

13.2 Animal Toxicology and/or Pharmacology

This study in juvenile rats with propranolol hydrochloride described above was intended to cover the period of development corresponding to infancy, childhood and adolescence. Neurologic effects including hypoactivity and delayed air righting reflex, increased germinal centers of lymph nodes, and increased white blood cells and lymphocytes were seen at a propranolol hydrochloride dose 45.6 mg/kg/day that represents a systemic exposure of 3 times that seen in children at the MRHD. Body weights were transiently decreased, and transient decreases in urine volume were associated with higher incidences of minimal renal cysts and dilation of kidney tubules at doses about equal to the MRHD in children.

14 CLINICAL STUDIES

A randomized, double-blind study in 460 infants, aged 35 days to 5 months at inclusion, with proliferating infantile hemangiomas (IH) requiring systemic therapy (excluding life-threatening IH, function-threatening IH, and ulcerated IH with pain and lack of response to simple wound care measures) compared four regimens of HEMANGEOL (1.2 or 3.4 mg/kg/day in twice daily divided doses for 3 or 6 months; N=99-103 per group) to placebo (N=55). Clinical efficacy was evaluated by counting complete or nearly complete resolution of the target hemangioma, which was evaluated by blinded centralized independent assessments of photographs at Week 24 compared to baseline.

Demographic patient characteristics and hemangioma characteristics were similar among the five regimens. For the whole population, 29% were male, 37% were in the lower age group (35-90 days), and 72% were Caucasian. Overall, 70% had a target hemangioma on the head, most commonly cheek (13%) and forehead (11%).

The main reason for treatment discontinuation was the treatment inefficacy, which happened in 58% of patients randomized to placebo, 25-30% of patients randomized to HEMANGEOL for 3 months (mainly after the switch to placebo), and 7-9% of patients randomized to HEMANGEOL for 6 months.

Overall, 2 out of 55 patients (4%) in the placebo arm and 61 out of 101 patients (60%) on HEMANGEOL 3.4 mg/kg/day for 6 months had complete or nearly complete resolution of their hemangioma at Week 24 (p <0.0001).

There were no significant differences in response by age (35-90 days / 91-150 days), sex, or hemangioma site. There were too few non-Caucasians to assess differences in effects by race.

Of patients on HEMANGEOL 3.4 mg/kg/day for 6 months who were considered successes, 10% required retreatment for recurrence of hemangiomas.

A second uncontrolled study in 23 patients with proliferating IH included function-threatening IH, IH in certain anatomic locations that often leave permanent scars or deformity, large facial IH, smaller IH in exposed areas, severe ulcerated IH, pedunculated IH. Target lesions resolved in 36% of patients by 3 months.

16 HOW SUPPLIED/STORAGE AND HANDLING

16.1 How Supplied

HEMANGEOL is supplied as an oral solution. Each 1 mL contains 4.28 mg propranolol.
HEMANGEOL is supplied in a carton containing one 120 mL bottle with syringe adapter and one 5-mL oral dosing syringe.

NDC 64370-375-01 Bottle 120 mL

16.2 Storage and Handling

Store at 25 °C (77 °F); excursions permitted from 15° to 30 °C (59° to 86 °F). [See USP Controlled Room Temperature.] Do not freeze.
Do not shake the bottle before use.
Dispense in original container with enclosed oral dosing syringe. The product can be kept for 2 months after first opening.
See instructions for using enclosed oral dosing syringe.

17 PATIENT COUNSELING INFORMATION

See FDA-approved patient labeling (Medication Guide and Instructions for Use).

Patient advice

Advise parents or caregivers to read the FDA-approved patient labeling (Medication Guide and Instructions for Use).

Instructions for using oral dosing syringe

Instruct parents or caregivers on use of the oral dosing syringe.

Risk of hypoglycemia

Inform parents or caregivers that there is a risk of hypoglycemia while on HEMANGEOL.
Hypoglycemia can occur at any time during treatment. Instruct caregivers to skip dosing in patients who are fasting (e.g., poor oral food intake, infection, vomiting), or when glucose demands are increased (e.g., cold, stress, infections). Instruct parents or caregivers how to recognize the signs of hypoglycemia. Tell them to discontinue HEMANGEOL if hypoglycemia develops and call their health care provider immediately or take the child to the emergency room. [see Warnings and Precautions 5.1]

Cardiovascular risks

Advise parents or caregivers that there is a potential risk for bradycardia, aggravation of pre-existing conduction disorders, and hypotension associated with the use of HEMANGEOL. Instruct them to contact their healthcare provider in case of fatigue, pallor, slow or uneven heart beats, peripheral coldness or fainting.

Respiratory risks

Inform parents or caregivers that HEMANGEOL carries risk of bronchospasm or exacerbation of lower respiratory tract infections. Instruct them to contact their healthcare provider or go to the nearest hospital emergency room if their child has breathing problems or wheezing during treatment with HEMANGEOL.

Other risks

Inform parents or caregivers that changes in sleep patterns may occur during HEMANGEOL therapy.

Ask parents or caregivers to tell you all the medications they are administering to their child including prescription and over the counter medicines, vitamins, and herbal supplements. Ask breastfeeding mothers to tell you all the medications they are currently taking, as these may pass into the milk.

MEDICATION GUIDE

HEMANGEOL® (he-man je-ohl)

(propranolol hydrochloride oral solution)

What is the most important information I should know about HEMANGEOL?

HEMANGEOL can cause serious side effects, including:

- Low blood sugar (hypoglycemia), especially if your child is not taking feedings, or is vomiting. HEMANGEOL may make it more difficult to recognize the signs and symptoms of low blood sugar in your child.

To help reduce the risk of low blood sugar with HEMANGEOL:

- Give HEMANGEOL during or shortly after feeding your child.
- Feed your child regularly during treatment. Tell your doctor if your child has a poor appetite.
- If your child is not taking feedings, for example, due to an illness or vomiting, do not give HEMANGEOL until your child is taking feedings normally again.

If your child has any of the signs or symptoms of low blood sugar listed below during treatment with HEMANGEOL, stop giving your child HEMANGEOL, call your healthcare provider immediately or go to the emergency room. If the child is conscious, give him/her a drink of liquid containing sugar.

Signs or symptoms of low blood sugar include: pale, blue or purple skin color, sweating, irritability, crying for no apparent reason, irregular or fast heartbeat, poor feeding, low body temperature, unusual sleepiness, seizures, breathing stops for short periods of time, and loss of consciousness.

What is HEMANGEOL?

HEMANGEOL is a prescription medicine used to treat proliferating infantile hemangioma that requires treatment with a medicine that spreads throughout the body.

Who should not take HEMANGEOL?

Do not give HEMANGEOL to your child if your child:

- was born prematurely and has not reached the corrected age of 5 weeks
- weighs less than 4 ½ pounds
- is allergic to propranolol or any of the other ingredients in HEMANGEOL. See the end of this Medication Guide for a list of ingredients in HEMANGEOL
- has asthma or a history of breathing problems
- has a heart problem, slow heart rate (less than 80 heart beats per minute), very low blood pressure
- is at risk for low blood sugar, for example is vomiting or unable to take feedings
- has high blood pressure caused by a tumor on the adrenal gland, called “pheochromocytoma”

What should I tell my doctor before giving my child HEMANGEOL?

Before you start giving HEMANGEOL to your child, tell your child’s doctor about all of your child’s
medical conditions.

Tell your doctor about all of the medicines that your child takes, including prescription and over-the-counter medicines, vitamins, and herbal supplements. HEMANGEOL and some medicines may interact with each other and cause serious side effects. Especially tell your doctor if your child takes a steroid medicine. Taking a steroid medicine during treatment with HEMANGEOL may increase your child’s risk of low blood sugar.

If you are breastfeeding your child, it is important to tell your doctor about all the medicines you take. Certain medicines may pass to your child through your breast-milk and interact with HEMANGEOL. Your doctor should tell you if you should stop breastfeeding.

How should I give HEMANGEOL to my child?

Follow the detailed Instructions for Use that come with HEMANGEOL for information about the correct way to prepare and give a dose of HEMANGEOL.

- Give HEMANGEOL to your child exactly as your doctor tells you.
- Your doctor may change the dose until it is right for your child, and as your child’s weight changes.
- Always give HEMANGEOL with a feeding or right away after a feeding.
- HEMANGEOL is given 2 times each day, at least 9 hours apart.
- If your child spits up a dose or if you are not sure your child got all of the medicine, do not give another dose. Wait until the next scheduled dose.

What are the possible side effects of HEMANGEOL?

See “ What is the most important information I should know about HEMANGEOL?”

HEMANGEOL can cause serious side effects, including:

- New or worsening slow heart rate (bradycardia) or low blood pressure (hypotension). Call your doctor if your child has any of these symptoms: pale skin color, slow or uneven heartbeats, arms or legs feel cold, blue or purple skin color, or fainting.
- Breathing problems or wheezing. HEMANGEOL can cause spasms of your child’s airway. Call your doctor or go to the nearest hospital emergency room if your child has breathing problems or wheezing during treatment with HEMANGEOL.
- Stroke. HEMANGEOL may increase the risk of stroke in certain children who have severe problems with the blood vessels in their brain, particularly if your child has a large hemangioma that affects the face or head.

The most common side effects include: sleep problems, worsening respiratory tract infections, diarrhea, and vomiting.

These are not all the possible side effects of HEMANGEOL. Call your doctor for medical advice about side effects. You may report side effects to FDA at 1-800-FDA-1088.

How should I store HEMANGEOL?

- Store HEMANGEOL at room temperature between 68o F to 77o F (20o C to 25o C). Do not freeze. Do not shake before use.
- Safely throw away any opened bottle of HEMANGEOL after 2 months, even if there is medicine left in the bottle.

Keep HEMANGEOL and all medicines out of the reach of children.

General information about the safe and effective use of HEMANGEOL.

Medicines are sometimes prescribed for purposes other than those listed in a Medication Guide. You can ask your pharmacist or doctor for information about HEMANGEOL that is written for health professionals. Do not use HEMANGEOL for a condition for which it was not prescribed. Do not give HEMANGEOL to other people, even if they have the same symptoms your child has. It may harm them.

What are the ingredients in HEMANGEOL?

Active ingredient: propranolol hydrochloride

Inactive ingredients: strawberry flavor, vanilla flavor, hydroxyethylcellulose, saccharin sodium, citric acid monohydrate, and water.

Manufactured for: Pierre Fabre Pharmaceuticals, Inc., Parsippany, NJ 07054

For more information, call 1-855-PFPHARM (737-4276)

This Medication Guide has been approved by the U.S. Food and Drug Administration Issued: Jun 2021

Instructions for Use

HEMANGEOL ® (he-man je-ohl)

(propranolol hydrochloride oral solution)

Read these Instructions for Use before giving a dose of HEMANGEOL to your child for the first time and each time you get a refill. There may be new information. Your doctor or pharmacist should show you how to correctly measure and give a dose of HEMANGEOL to your child before you give it for the first time.

Important: Read the Medication Guide that comes with HEMANGEOL.

- To reduce the risk of your child getting low blood sugar (hypoglycemia), you must give HEMANGEOL either during a feeding or right away after a feeding.
- Do not give a dose of HEMANGEOL if your child is vomiting, is not taking feedings, or is showing signs or symptoms of low blood sugar.

When you get HEMANGEOL from your doctor or pharmacist, you will receive a box that contains the supplies needed to give HEMANGEOL to your child, including:

- One glass bottle of HEMANGEOL
- One 5 mL oral dosing syringe (inside a plastic bag) that is marked to help you correctly measure a dose of HEMANGEOL (See Figure A). If the carton does not contain the oral dosing syringe, ask your pharmacist to give you an oral dosing syringe that can be used to measure HEMANGEOL.

Figure A

Preparing to give your child a dose of HEMANGEOL:

Step 1. Place your box of supplies on a clean flat work surface, such as a table.

Step 2. Remove the HEMANGEOL bottle and oral dosing syringe from the box (See Figure A above). Do not shake the bottle before use. Keep the box for storage.

Step 3. Remove the oral dosing syringe from the plastic bag. Safely throw the plastic bag away. The barrel of the syringe has markings in milliliters (mL). Look at the markings on the barrel of the oral dosing syringe and find the mL marking that matches the HEMANGEOL dose in mL prescribed by your doctor (See Figure B).

Figure B

Step 4. Open the bottle of HEMANGEOL by pushing down on the plastic cap while turning the cap to the left (See Figure C).

- Write down on the box the date when you first open the bottle.

Figure C

Step 5. Place the bottle on your work surface. Use one hand to hold the bottle upright.Use your other hand to insert the tip of the oral dosing syringe into the syringe adapter at the top of the bottle. Push the plunger all the way down (See Figure D).

- Do not remove the syringe adapter. If the syringe adapter is missing talk to your pharmacist.

Figure D

Step 6: Use one hand to hold the oral dosing syringe in place. With your other hand, turn the bottle upside down. Pull back on the plunger until the top of the plunger lines up with the marking on the barrel of the syringe that matches the dose of HEMANGEOL prescribed by your doctor (See Figure E). Your child’s dose may be different than the dose shown in Figure E.

Figure E

Step 7: Check for air bubbles in the oral dosing syringe. If you see air bubbles, push up on the plunger towards the bottle just enough to remove any large air bubbles and then pull back to the measured dose (See Figure F).

Figure F

Step 8. Turn bottle upright again and place it in on your work surface. Remove the oral dosing syringe from the bottle (See Figure G). Do not push the plunger in during this step. The syringe adapter should stay attached to the bottle.

Figure G

Giving your child a dose of HEMANGEOL:

Step 9. Slowly squirt HEMANGEOL into your child’s mouth after placing the oral dosing syringe against the inside of the cheek (See Figure H).

- Keep your child in an upright position for a few minutes right after giving a dose of HEMANGEOL.

Figure H

- If needed, you can dilute the dose of HEMANGEOL in a small amount of milk or fruit juice and give it to your child in a baby’s bottle. If your child spits up a dose or if you are not sure your child got all of the medicine, do not give another dose. Wait until the next scheduled dose.

Step 10. Replace the plastic cap on the bottle. Close the bottle by turning the plastic cap to the right (See Figure I).

Figure I

Cleaning the oral dosing syringe:

Step 11: Clean the oral dosing syringe after each use by rinsing with clean tap water (See Figure J).

- Do not take apart the oral dosing syringe.
- Do not use any soap or alcohol based product to clean. Wipe the outside dry.
- Do not put the oral dosing syringe through a sterilizer or dishwasher.

Figure J

Step 12: Place the bottle and the oral dosing syringe in the box.

How should I store HEMANGEOL?

- When not in use, keep the bottle of HEMANGEOL and the oral dosing syringe in the box it comes in.
- Store HEMANGEOL at room temperature, between 68o F to 77o F (20o C to 25o C). Do not freeze.
- Safely throw away any opened bottle of HEMANGEOL after 2 months, even if there is medicine left in the bottle.

Keep HEMANGEOL and all medicines out of the reach of children.

This Instructions for Use has been approved by the U.S. Food and Drug Administration.

Manufactured for:

Pierre Fabre Pharmaceuticals, Inc.

Parsippany, NJ 07054

PRINCIPAL DISPLAY PANEL - 120 mL Bottle Label

NDC 64370-375-01

Hemangeol ®

(propranolol hydrochloride)

oral solution

4.28 mg/mL

Dispense with enclosed Medication Guide

Rx only

120 mL

PRINCIPAL DISPLAY PANEL - 120 mL Carton Label

NDC 64370-375-01

Hemangeol ®

(propranolol hydrochloride)

oral solution

4.28 mg/mL

Pharmacist: Dispense the enclosed Medication Guide to each patient

Rx only

120 mL